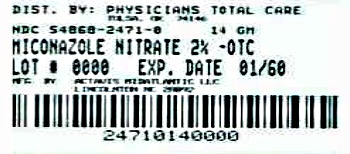 DRUG LABEL: Miconazole Nitrate
NDC: 54868-2471 | Form: CREAM
Manufacturer: Physicians Total Care, Inc.
Category: otc | Type: HUMAN OTC DRUG LABEL
Date: 20121105

ACTIVE INGREDIENTS: MICONAZOLE NITRATE 20 mg/1 g
INACTIVE INGREDIENTS: BENZOIC ACID; BUTYLATED HYDROXYANISOLE; MINERAL OIL; WATER

Miconazole Nitrate Antifungal Cream

ACTIVE INGREDIENT

Miconazole nitrate 2%

PURPOSE

Antifungal

USES

- treats most athlete’s foot, jock itch and ringworm
- relieves itching, scaling, burning, irritation and discomfort

WARNINGS

For external use only

WHEN USING THIS PRODUCT

- do not get into the eyes

STOP USE AND ASK A DOCTOR IF

- irritation occurs
- there is no improvement within 4 weeks (for athlete’s foot or ringworm) or within 2 weeks (for jock itch)

Do not use on children under 2 years, unless directed by a doctor.

KEEP OUT OF REACH OF CHILDREN

If swallowed, get medical help or contact a Poison Control Center right away.

DIRECTIONS

- clean the affected area and dry thoroughly
- apply a thin layer of the product over affected area twice daily (morning and night), or as directed by a doctor
- supervise children in the use of this product
- this product does not work on the scalp or nails

For athlete’s foot

- pay special attention to spaces between the toes; wear well-fitting, ventilated shoes, and change shoes and socks at least once every day
  For athlete’s foot and ringworm
- use every day for 4 weeks
  For jock itch
- use every day for 2 weeks. If condition lasts longer, contact a doctor.

OTHER INFORMATION

Store at room temperature 59º - 86ºF (15º - 30ºC).

IMPORTANT: The opening of this product is covered by a metal tamper-evident seal. If this seal has been punctured or is not visible, do not use and return product to place of purchase.

TO OPEN: To puncture the seal, reverse the cap and place the puncture-top onto the tube. Push firmly until seal is open. To close, screw the cap back onto the tube.

INACTIVE INGREDIENTS

Benzoic acid, BHA, mineral oil, peglicol 5 oleate, pegoxol 7 stearate, purified water

PACKAGE LABEL.PRINCIPAL DISPLAY PANEL

NDC 54868-2471-0

Compare to the active ingredient in Micatin® Antifungal Cream*

Actavis

Antifungal Cream

Miconazole Nitrate 2%

Relieves Burning, Cures Most Athlete’s Foot, Jock Itch, Ringworm

Net wt. 14 g tube cream

07350200D1 VC106266

Additional barcode labeling by:
Physicians Total Care, Inc.
Tulsa, Oklahoma 74146